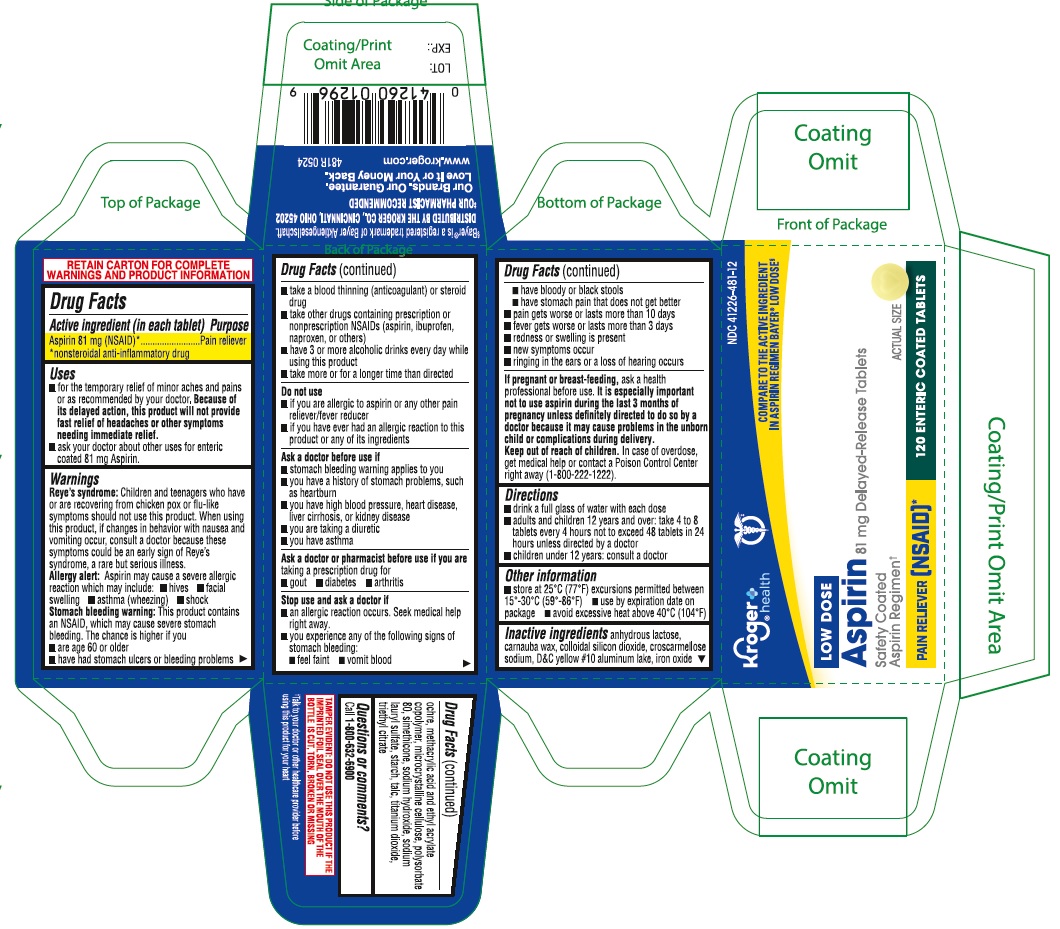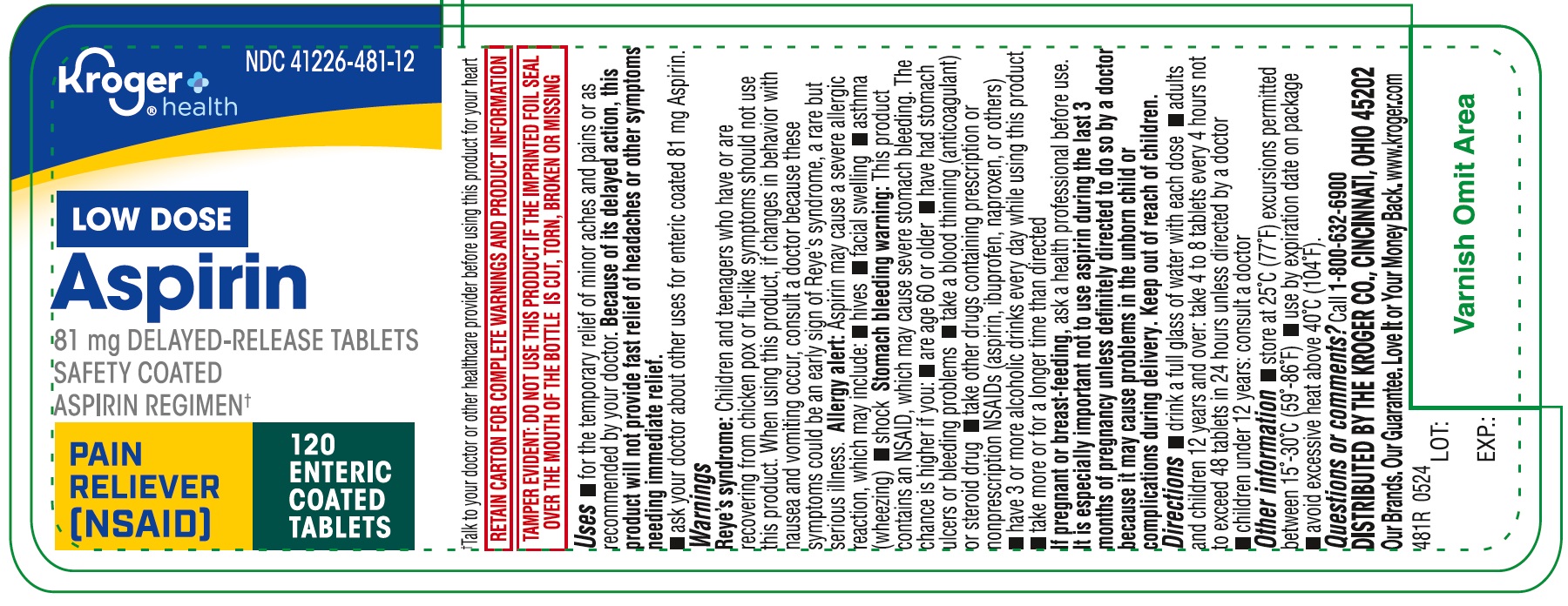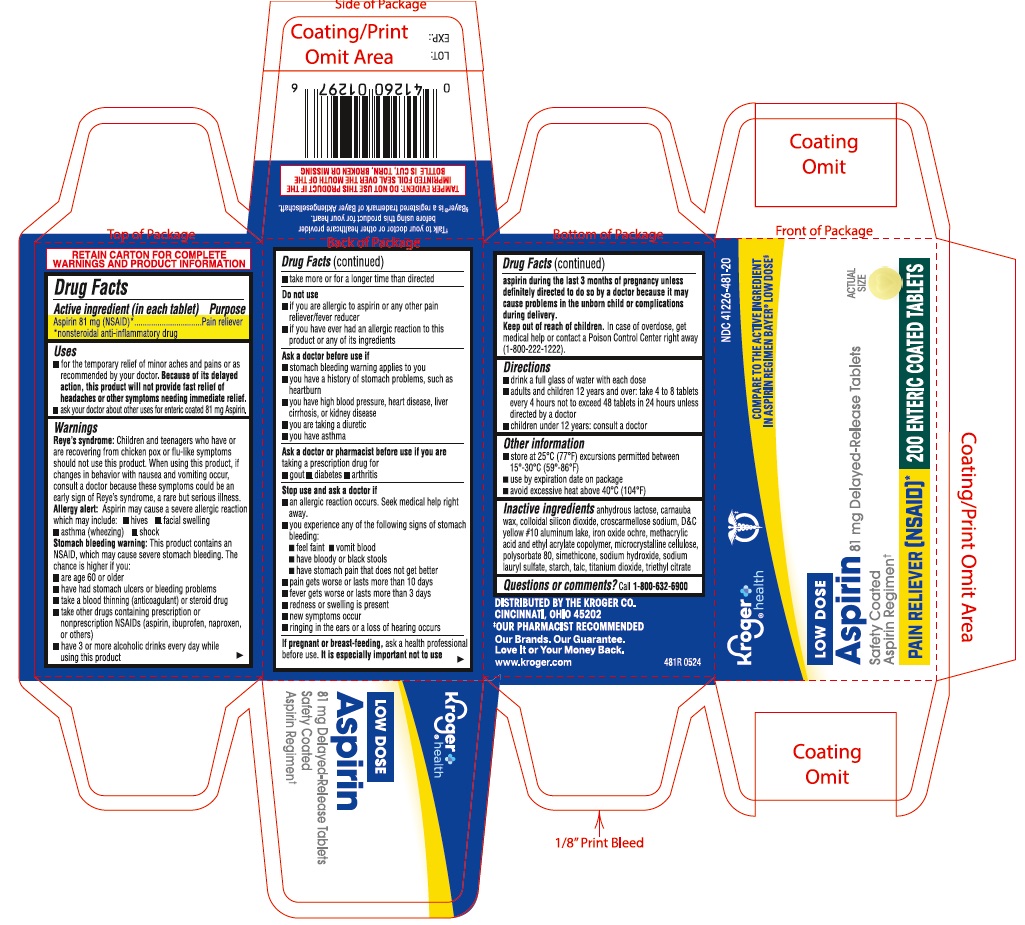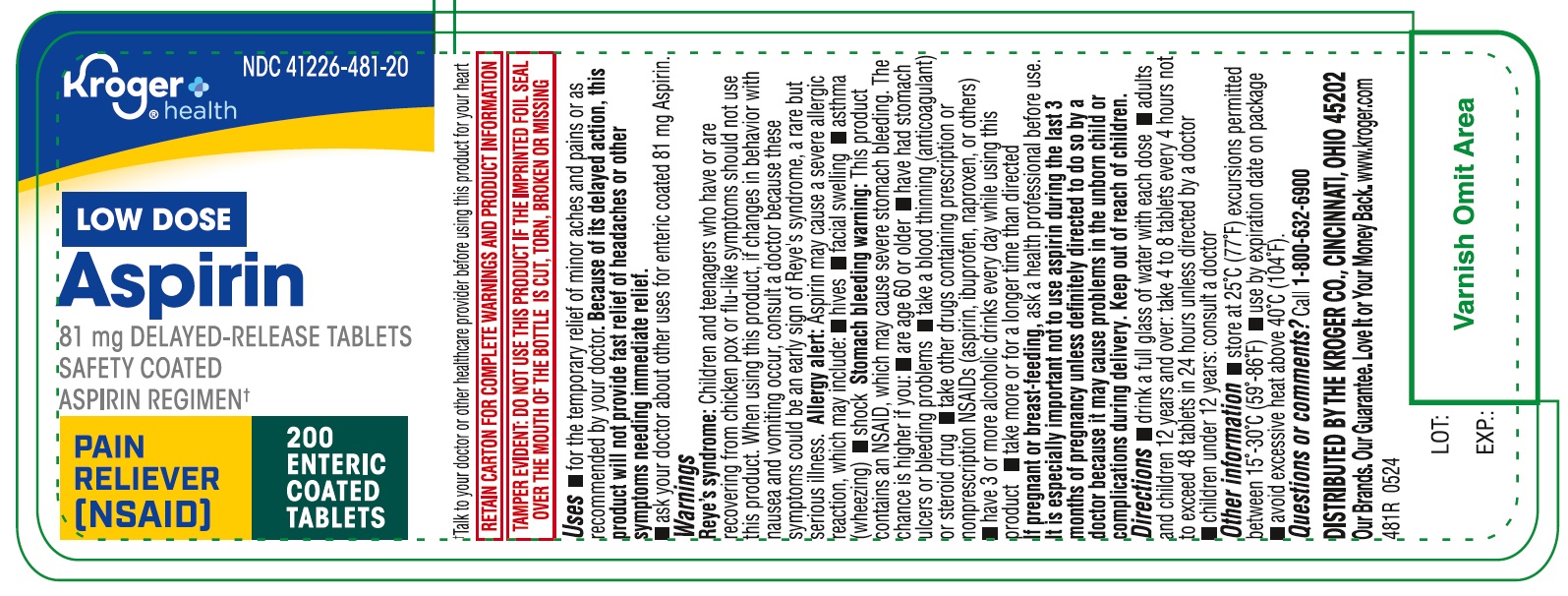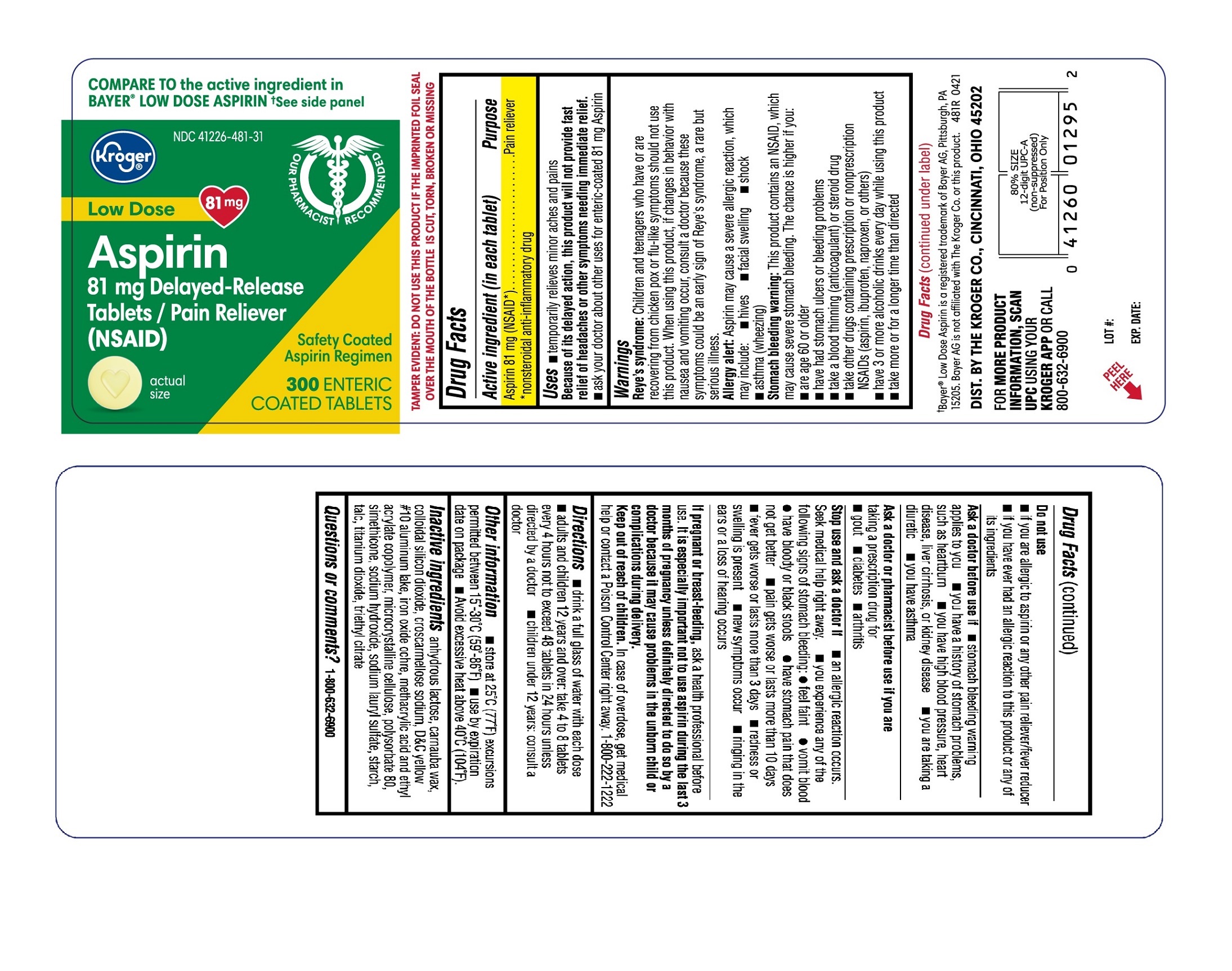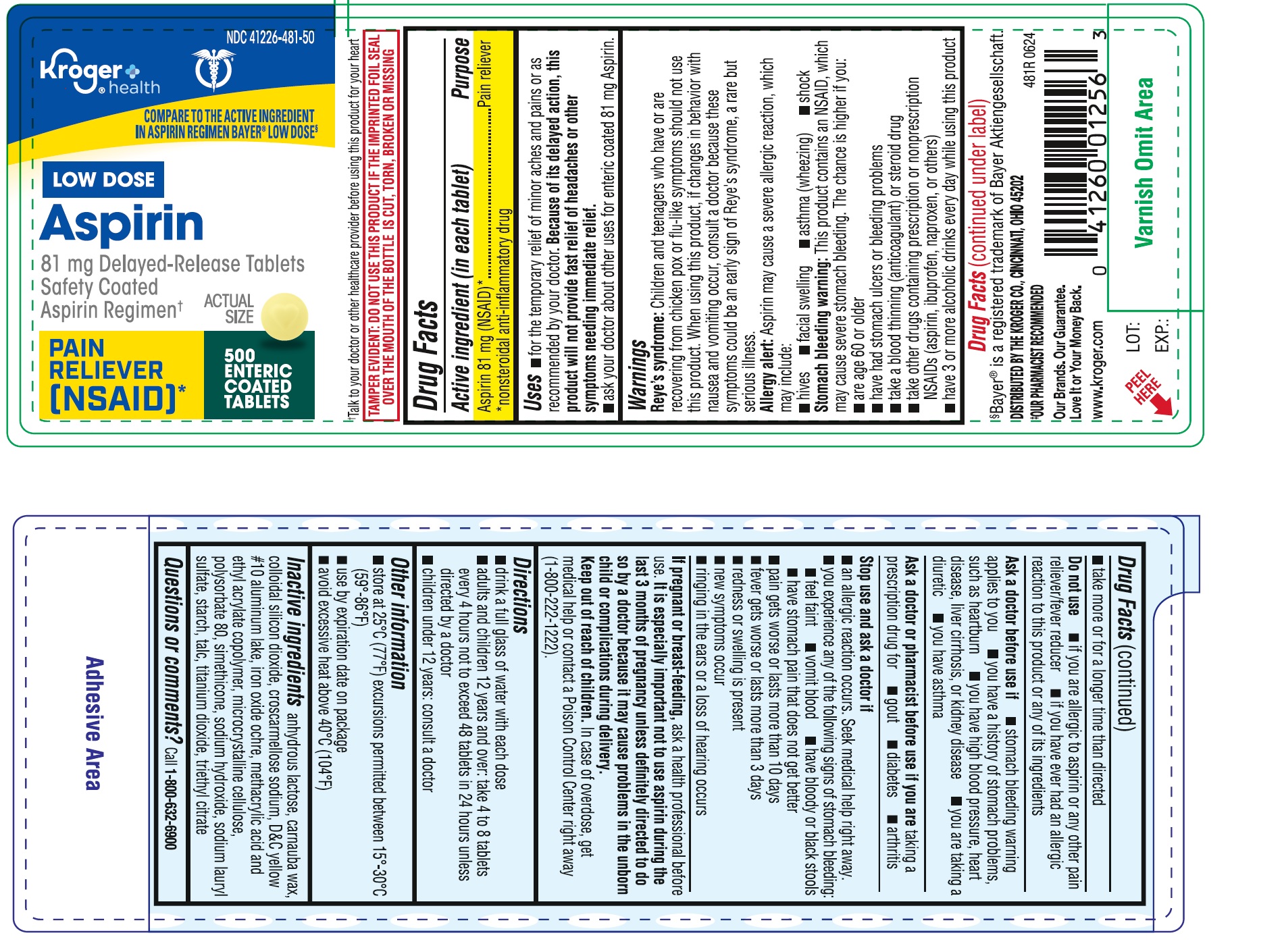 DRUG LABEL: ASPIRIN
NDC: 41226-481 | Form: TABLET, COATED
Manufacturer: Kroger Company
Category: otc | Type: HUMAN OTC DRUG LABEL
Date: 20250919

ACTIVE INGREDIENTS: ASPIRIN 81 mg/1 1
INACTIVE INGREDIENTS: ANHYDROUS LACTOSE; D&C YELLOW NO. 10 ALUMINUM LAKE; CARNAUBA WAX; DIMETHICONE; SODIUM HYDROXIDE; SILICON DIOXIDE; CROSCARMELLOSE SODIUM; MICROCRYSTALLINE CELLULOSE; SODIUM LAURYL SULFATE; TITANIUM DIOXIDE; TRIETHYL CITRATE; BROWN IRON OXIDE; METHACRYLIC ACID AND ETHYL ACRYLATE COPOLYMER; POLYSORBATE 80; STARCH, CORN; TALC

481R Kroger 41226-481 Aspirin 81 mg Delayed-Release Tablets

Active ingredient (in each tablet)
Aspirin 81 mg (NSAID*)

*nonsteroidal anti-inflammatory drug

Purpose
Pain reliever

Uses

- temporarily relieves minor aches and pains Because of its delayed action, this product will not provide fast relief of headaches or other symptoms needing immediate relief.
- ask your doctor about other uses for enteric-coated 81 mg Aspirin

Warnings
Reye’s syndrome: Children and teenagers who have or are recovering from chicken pox or flu-like symptoms should not use this product. When using this product, if changes in behavior with nausea and vomiting occur, consult a doctor because these symptoms could be an early sign of Reye's syndrome, a rare but serious illness.
Allergy alert: Aspirin may cause a severe allergic reaction, which may include:

- hives
- facial swelling
- shock
- asthma (wheezing)

Stomach bleeding warning: This product contains an NSAID, which may cause severe stomach bleeding.
The chance is higher if you:

- are age 60 or older
- have had stomach ulcers or bleeding problem
- take a blood thinning (anticoagulant) or steroid drug
- take other drugs containing prescription or nonprescription NSAIDs (aspirin, ibuprofen, naproxen, or others)
- have 3 or more alcoholic drinks every day while using this product
- take more or for a longer time than directed

Do not use

- if you are allergic to aspirin or any other pain reliever/fever reducer
- if you have ever had an allergic reaction to this product or any of its ingredients

Ask a doctor before use if

- stomach bleeding warning applies to you
- you have a history of stomach problems, such as heartburn
- you have high blood pressure, heart disease, liver cirrhosis, or kidney disease
- you are taking a diuretic
- you have asthma

Ask a doctor or pharmacist before use if you are taking a prescription drug for

- gout
- diabetes
- arthritis

Stop use and ask a doctor if

- an allergic reaction occurs. Seek medical help right away.
- you experience any of the following signs of stomach bleeding:

feel faint
vomit blood

have bloody or black stools
have stomach pain that does not get better

- pain gets worse or lasts more than 10 days
- fever gets worse or lasts more than 3 days
- redness or swelling is present
- new symptoms occur
- ringing in the ears or a loss of hearing occurs

PREGNANCY OR BREAST FEEDING

If pregnant or breast-feeding, ask a health professional before use. It is especially important not to use aspirin during the last 3 months of pregnancy unless definitely directed to do so by a doctor because it may cause problems in the unborn child or complications during delivery.

Keep out of reach of children. In case of overdose, get medical help or contact a Poison Control Center right away. 1-800-222-1222

Directions

- drink a full glass of water with each dose
- adults and children 12 years and over: take 4 to 8 tablets every 4 hours not to exceed 48 tablets in 24 hours unless directed by a doctor
- children under 12 years: consult a doctor

OTHER INFORMATION

- store at 25°C (77°F) excursions permitted between 15°-30°C (59°-86°F)
- use by expiration date on package
- avoid excessive heat above 40°C (104°F)

INACTIVE INGREDIENT

Inactive ingredients anhydrous lactose, carnauba wax, colloidal silicon dioxide, croscarmellose sodium, D&C yellow #10 aluminum lake, iron oxide ochre, methacrylic acid and ethyl acrylate copolymer, microcrystalline cellulose, polysorbate 80, simethicone, sodium hydroxide, sodium lauryl sulfate, starch, talc, titanium dioxide, triethyl citrate

Questions or comments? 1-800-632-6900